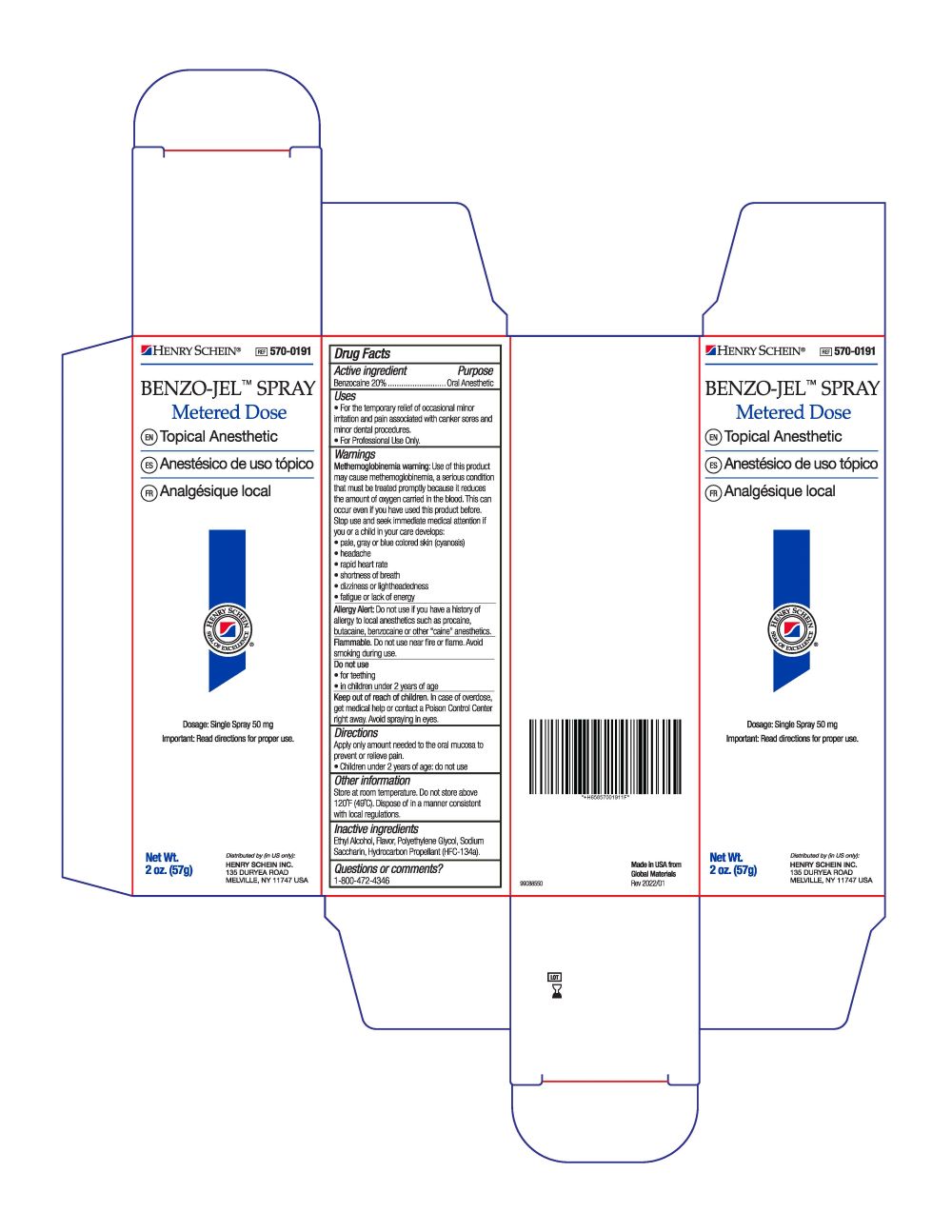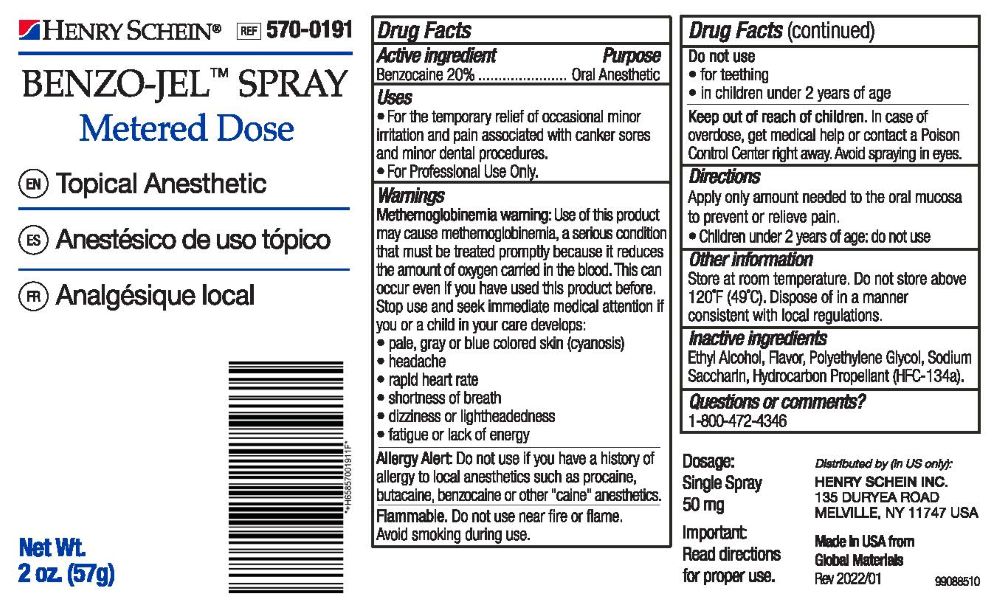 DRUG LABEL: Benzo Jel
NDC: 0404-0018 | Form: SPRAY, METERED
Manufacturer: Henry Schein Inc.
Category: otc | Type: HUMAN OTC DRUG LABEL
Date: 20240215

ACTIVE INGREDIENTS: BENZOCAINE 11.4 g/57 g
INACTIVE INGREDIENTS: ALCOHOL; POLYETHYLENE GLYCOL 400; SACCHARIN SODIUM

Active Ingredient

Benzocaine 20%

Purpose

Oral Anesthetic

Uses

- For the temporary relief of occasional minor irritation and pain associated with canker sores and minor dental procedures.
- For Professional Use Only.

Warnings

Methemoglobinemia warning: Use of this product may cause methemoglobinemia, a setious condition that must be treated promptiy because it reduces the amount of oxygen canied in the blood. This can occur even if you have used this product before. Slop use and seek immediate medical attention tt you or a child in your care develops:

• pale, gray or blue colored skn (cyanosis)
• headache
• rapid heart rate
• shortress of breath
• dizziness or lightheadedness
• fatigue or lack of energy

Allergy Alert: Do not use if you have a history of allergy to local anesthetics such as procaine, butacaine, benzocaine or other "caine" anesthetics.

Flammable. Do not use near fire or flame. Avoid smoking during use.

Do not use:

- for teething
- in children under 2 years of age

Keep out of reach of children. In case of overdose, get medical help or contact a Poison Control Center nght away. Avoid spraying in eyes.

Dosage

A single metered spray dispenses 50 mg of Benzo-Jel Topical Anesthetic. Use only as directed by a dentist.

Other information

Store at room temperature. Do not store above 120°F (49°C). Dispose of in a manner consistent with local regulations.

Inactive ingredients

Ethyl Alcohol, Flavor, Polyethelyn Glycol, Sodium Saccharin, Hydrocarbon Propellant (HFC-134a).

Questions or comments?

1-800-472-4346